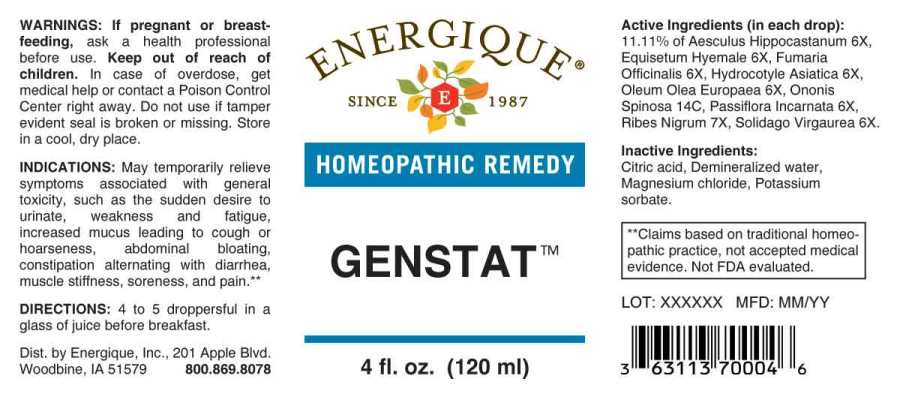 DRUG LABEL: Genstat
NDC: 44911-0520 | Form: LIQUID
Manufacturer: Energique, Inc.
Category: homeopathic | Type: HUMAN OTC DRUG LABEL
Date: 20230712

ACTIVE INGREDIENTS: HORSE CHESTNUT 6 [hp_X]/1 mL; EQUISETUM HYEMALE WHOLE 6 [hp_X]/1 mL; FUMARIA OFFICINALIS FLOWERING TOP 6 [hp_X]/1 mL; CENTELLA ASIATICA WHOLE 6 [hp_X]/1 mL; OLIVE OIL 6 [hp_X]/1 mL; PASSIFLORA INCARNATA FLOWERING TOP 6 [hp_X]/1 mL; RIBES NIGRUM LEAF 7 [hp_X]/1 mL; SOLIDAGO VIRGAUREA FLOWERING TOP 6 [hp_X]/1 mL; ONONIS SPINOSA WHOLE 14 [hp_C]/1 mL
INACTIVE INGREDIENTS: ANHYDROUS CITRIC ACID; MAGNESIUM CHLORIDE; POTASSIUM SORBATE

Drug Facts:

ACTIVE INGREDIENTS:

(in each drop): 11.11% of Aesculus Hippocastanum 6X, Equisetum Hyemale 6X, Fumaria Officinalis 6X, Hydrocotyle Asiatica 6X, Oleum Olea Europaea 6X, Ononis Spinosa 14C, Passiflora Incarnata 6X, Ribes Nigrum 7X, Solidago Virgaurea 6X.

INDICATIONS:

May temporarily relieve symptoms associated with general toxicity, such as the sudden desire to urinate, weakness and fatigue, increased mucus leading to cough or hoarseness, abdominal bloating, constipation alternating with diarrhea, muscle stiffness, soreness and pain.**

**Claims based on traditional homeopathic practice, not accepted medical evidence. Not FDA evaluated.

WARNINGS:

If pregnant or breastfeeding, ask a health professional before use.

Keep out of reach of children. In case of overdose, get medical help or contact a Poison Control Center right away.

Do not use if tamper evident seal is broken or missing.

Store in a cool, dry place.

Keep out of reach of children. In case of overdose, get medical help or contact a Poison Control Center right away.

DIRECTIONS:

4 to 5 droppersful in a glass of juice before breakfast.

INDICATIONS:

May temporarily relieve symptoms associated with general toxicity, such as the sudden desire to urinate, weakness and fatigue, increased mucus leading to cough or hoarseness, abdominal bloating, constipation alternating with diarrhea, muscle stiffness, soreness and pain.**

**Claims based on traditional homeopathic practice, not accepted medical evidence. Not FDA evaluated.

INACTIVE INGREDIENTS:

Citric acid, Demineralized water, Magnesium chloride, Potassium sorbate

QUESTIONS:

Dist. by Energique, Inc., 201 Apple Blvd.
Woodbine, IA 51579 800.869.8078

PACKAGE LABEL DISPLAY:

ENERGIQUE
SINCE 1987
HOMEOPATHIC REMEDY
GENSTAT
4 fl. oz. (120 ml)